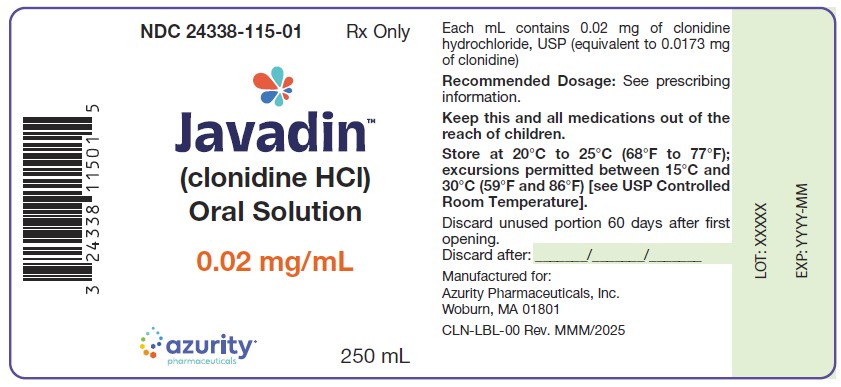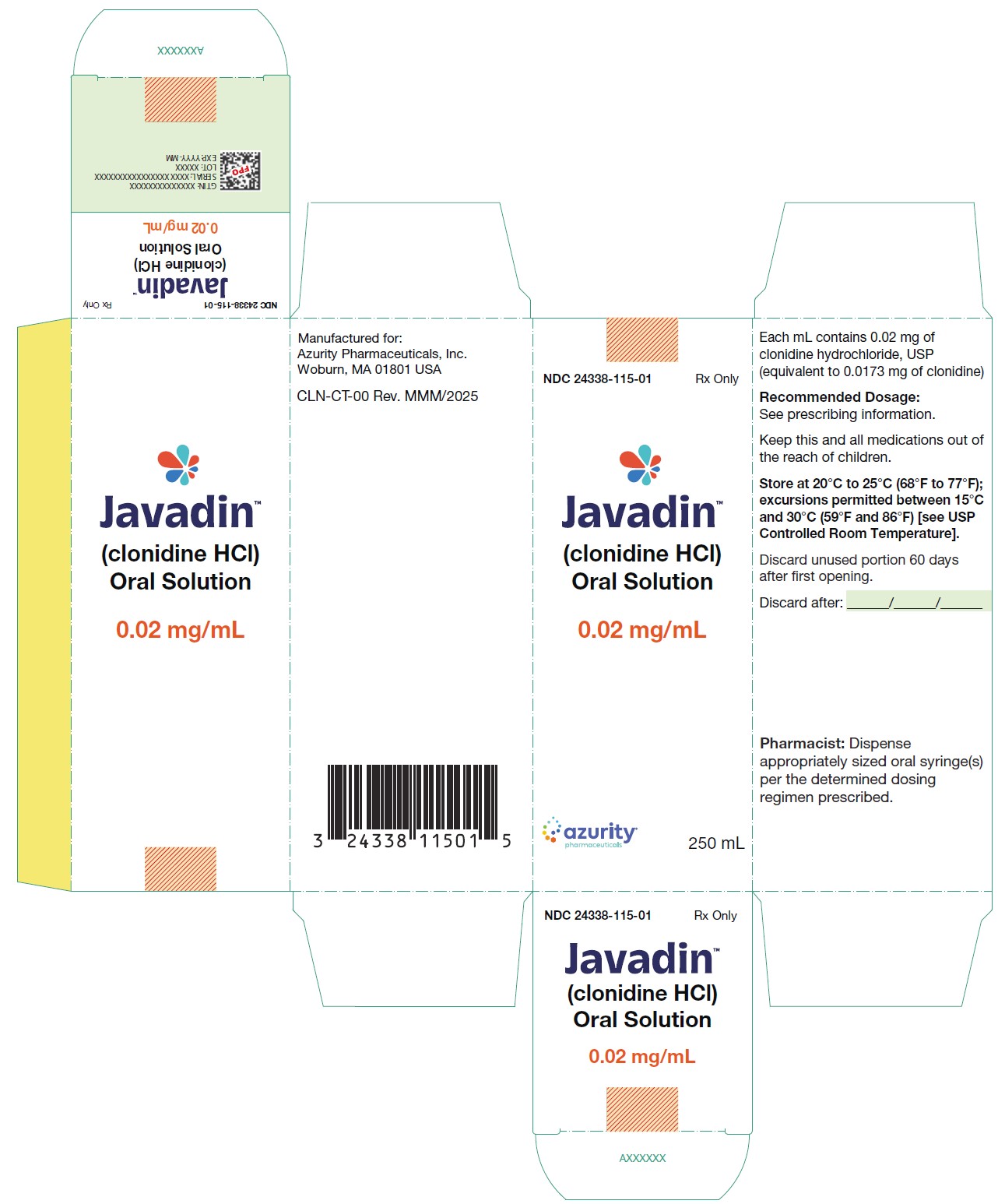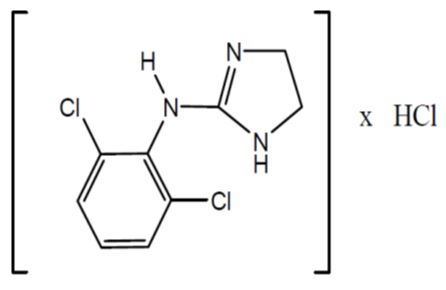 DRUG LABEL: JAVADIN
NDC: 24338-115 | Form: SOLUTION
Manufacturer: Azurity Pharmaceuticals, Inc.
Category: prescription | Type: Human Prescription Drug Label
Date: 20251024

ACTIVE INGREDIENTS: CLONIDINE HYDROCHLORIDE 20 ug/1 mL
INACTIVE INGREDIENTS: SODIUM CHLORIDE; SUCRALOSE; SODIUM PROPIONATE; SODIUM HYDROXIDE; HYDROCHLORIC ACID

HIGHLIGHTS OF PRESCRIBING INFORMATION

These highlights do not include all the information needed to use JAVADIN safely and effectively. See full prescribing information for JAVADIN.
JAVADINTM(clonidine hydrochloride) oral solution
Initial U.S. Approval: 1974

1 INDICATIONS AND USAGE

- JAVADIN is a central alpha-2 adrenergic agonist, indicated for the treatment of hypertension in adult patients to lower blood pressure. Lowering blood pressure has been shown to reduce the risk of fatal and nonfatal cardiovascular events, primarily strokes and myocardial infarctions. (1)

2 DOSAGE AND ADMINISTRATION

- Initial dosage is 0.1 mg orally twice daily with or without food (morning and bedtime) (2.1)
- Titrate in increments of 0.1 mg per day at weekly intervals if necessary until the desired response is achieved. (2.1)
- The therapeutic doses most commonly used have ranged from 0.2 mg to 0.6 mg per day, given in divided doses. (2.1)
- Maximum recommended daily dose is 2.4 mg. (2.1)

3 DOSAGE FORMS AND STRENGTHS

• Oral Solution: 0.02 mg/mL (3)

4 CONTRAINDICATIONS

• JAVADIN is contraindicated in patients with known hypersensitivity to clonidine (4)

5 WARNINGS AND PRECAUTIONS

- Bradycardia, Cardiac Conduction Abnormalities, and Symptomatic Hypotension: Clonidine may cause bradycardia, conduction abnormalities, and hypotension. Titrate slowly in patients with syncope, heart block, or vascular disease. Monitor blood pressure and heart rate. Avoid drugs affecting sinus or AV node function. (5.1)
- Rebound Hypertension: Abrupt discontinuation of JAVADIN may cause rebound hypertension, especially with high doses or beta-blocker use. Taper gradually over 2–4 days. Continue administration up to 4 hours before surgery and resume promptly postoperatively; monitor blood pressure closely. (5.2)
- Sedation and Somnolence: Clonidine may cause sedation; caution patients who operate machinery or drive. (5.3)

6 ADVERSE REACTIONS

- The most frequent adverse reactions are dry mouth, drowsiness, dizziness, constipation and sedation. (6.1)

To report SUSPECTED ADVERSE REACTIONS, contact Azurity Pharmaceuticals, Inc., at 1-800-461-7449 or FDA at 1-800-FDA-1088 or www.fda.gov/medwatch.

7 DRUG INTERACTIONS

- Sedating Drugs: Clonidine may potentiate the CNS-depressive effects of alcohol, barbiturates or other sedating drugs. (7)
- Tricyclic Antidepressants: May reduce the hypotensive effect of clonidine. (7)
- Neuroleptics: May induce or exacerbate the orthostatic regulation disturbances (e.g., orthostatic hypotension, dizziness, fatigue). (7)
- Drugs Known to Affect Sinus Node Function or AV Nodal Conduction: Caution is warranted in patients receiving clonidine concomitantly with agents known to affect sinus node function or AV nodal conduction (e.g., digitalis, calcium channel blockers and beta-blockers) due to a potential for additive effects such as bradycardia and AV block. (7)

8 USE IN SPECIFIC POPULATIONS

- Renal Impairment: Patients with renal impairment may require a lower initial dose and should be closely monitored. (8.6)

FULL PRESCRIBING INFORMATION

1 INDICATIONS AND USAGE

JAVADIN is indicated for the treatment of hypertension in adult patients, to lower blood pressure. Lowering blood pressure reduces the risk of fatal and nonfatal cardiovascular events, primarily strokes and myocardial infarctions. These benefits have been seen in controlled trials of antihypertensive drugs from a wide variety of pharmacologic classes. There are no controlled trials demonstrating risk reduction with JAVADIN.
Control of high blood pressure should be part of comprehensive cardiovascular risk management, including, as appropriate, lipid control, diabetes management, antithrombotic therapy, smoking cessation, exercise, and limited sodium intake. Many patients will require more than one drug to achieve blood pressure goals. For specific advice on goals and management, see published guidelines, such as those of the National High Blood Pressure Education Program’s Joint National Committee on Prevention, Detection, Evaluation, and Treatment of High Blood Pressure (JNC).
Numerous antihypertensive drugs, from a variety of pharmacologic classes and with different mechanisms of action, have been shown in randomized controlled trials to reduce cardiovascular morbidity and mortality, and it can be concluded that it is blood pressure reduction, and not some other pharmacologic property of the drugs, that is largely responsible for those benefits. The largest and most consistent cardiovascular outcome benefit has been a reduction in the risk of stroke, but reductions in myocardial infarction and cardiovascular mortality also have been seen regularly.
Elevated systolic or diastolic pressure causes increased cardiovascular risk, and the absolute risk increase per mmHg is greater at higher blood pressures, so that even modest reductions of severe hypertension can provide substantial benefit. Relative risk reduction from blood pressure reduction is similar across populations with varying absolute risk, so the absolute benefit is greater in patients who are at higher risk independent of their hypertension (for example, patients with diabetes or hyperlipidemia), and such patients would be expected to benefit from more aggressive treatment to a lower blood pressure goal.
Some antihypertensive drugs have smaller blood pressure effects (as monotherapy) in black patients, and many antihypertensive drugs have additional approved indications and effects (e.g., on angina, heart failure, or diabetic kidney disease). These considerations may guide selection of therapy.
JAVADIN may be used alone or in combination with other antihypertensive agents.

2 DOSAGE AND ADMINISTRATION

2.1 Recommended Dosage

Dosage should be individualized based on response. The recommended initial dosage is 0.1 mg orally twice daily (morning and bedtime).
Dosage can be titrated in increments of 0.1 mg per day at weekly intervals as necessary. Doses should be taken twice a day, with either an equal or higher split dosage being given at bedtime. The therapeutic doses most commonly employed have ranged from 0.2 mg to 0.6 mg per day, given in divided doses. Maximum recommended daily dose is 2.4 mg, but doses as high as this have rarely been employed.

2.2 Administration Instructions

A calibrated measuring device, such as an oral dosing syringe or oral dosing cup, is recommended to measure and deliver the prescribed dose accurately. A household teaspoon or tablespoon is not an adequate measuring device.
Administer JAVADIN (clonidine hydrochloride) oral solution with or without food. [see Clinical Pharmacology (12.3)]
JAVADIN may be administered up to 4 hours before surgery and resume as soon as possible post-operatively [see Warning and Precaution (5.2)].

3 DOSAGE FORMS AND STRENGTHS

Oral Solution: 0.02 mg/mL clear, colorless solution, with mixed-berry flavor.

4 CONTRAINDICATIONS

JAVADIN is contraindicated in patients with known hypersensitivity to clonidine. [see Adverse Reactions (6)].

5 WARNINGS AND PRECAUTIONS

5.1 Bradycardia, Cardiac Conduction Abnormalities, and Symptomatic Hypotension

Treatment with clonidine can cause bradycardia, cardiac conduction abnormalities, and symptomatic hypotension [see Adverse Reactions (6.1)]. The sympatholytic action of clonidine may worsen sinus node dysfunction and atrioventricular (AV) block, especially in patients taking other sympatholytic drugs. There have been post-marketing reports of patients with conduction abnormalities and/or taking other sympatholytic drugs who developed severe bradycardia requiring intravenous (IV) atropine, IV isoproterenol, and temporary cardiac pacing while taking clonidine.
Titrate JAVADIN slowly in patients with a history of syncope, cardiac conduction abnormalities, and those with underlying conditions that may be worsened by hypotension and bradycardia; e.g., heart block, bradycardia, cardiovascular disease, vascular disease, cerebrovascular disease, or chronic renal failure. Monitor blood pressure and heart rate and adjust dosages accordingly in patients treated concomitantly with antihypertensives or other drugs that can reduce blood pressure or heart rate or increase the risk of syncope Avoid the use of drugs that can affect the sinus node function or AV node conduction [see Drug Interactions (7)].
In patients who have a history of syncope or may have a condition that predisposes them to syncope, such as symptomatic hypotension, bradycardia, or dehydration, advise patients to avoid becoming dehydrated or overheated.

5.2 Rebound Hypertension

Abrupt discontinuation of JAVADIN can cause rebound hypertension with elevated plasma catecholamines, especially with higher doses or concomitant beta-blocker use. Symptoms of abrupt discontinuation include tachycardia, rapid blood pressure elevation, headache, nervousness, and agitation. Serious cases of hypertensive encephalopathy, stroke, and death have been reported after abrupt clonidine discontinuation. To reduce the risk of rebound hypertension, taper clonidine gradually over 2-4 days. If rebound hypertension occurs, reverse hypertensive crisis with oral clonidine or IV phentolamine. When discontinuing concurrent beta-blocker therapy, withdraw the beta-blocker several days before beginning clonidine taper.
Administration of JAVADIN should be continued up to 4 hours before surgery and resumed as soon as possible thereafter. Blood pressure should be carefully monitored during surgery and additional measures to control blood pressure should be available if required.

5.3 Sedation and Somnolence

Clonidine may cause sedation. Patients who engage in potentially hazardous activities, such as operating machinery or driving, should be advised of possible sedative effects of clonidine. Avoid use with other central nervous system (CNS) depressants, as this combination may cause excessive drowsiness or sedation [see Drug Interactions (7)].

6 ADVERSE REACTIONS

The following clinically significant adverse reactions are discussed elsewhere in the labeling:

- Bradycardia, Cardiac Conduction Abnormalities, and Symptomatic Hypotension [see Warnings and Precautions (5.1)]
- Rebound Hypertension [see Warnings and Precautions (5.2)]
- Sedation and Somnolence [see Warnings and Precautions (5.3)]

6.1 Clinical Trial Experience

Because clinical trials are conducted under widely varying conditions, adverse reaction rates observed in the clinical trials of a drug cannot be directly compared to rates in the clinical trials of another drug and may not reflect the rates observed in practice.
Most adverse effects are mild and tend to diminish with continued therapy. The most frequent (which appear to be dose-related) are dry mouth (40%), drowsiness (33%); dizziness (16%); constipation and sedation (10%, respectively).
The following less frequent adverse experiences have also been reported in patients receiving clonidine hydrochloride tablets, but in many cases patients were receiving concomitant medication and a causal relationship has not been established.
Body as a Whole: Fatigue, headache, pallor, malaise, weakness, and withdrawal syndrome.
Cardiovascular: Bradycardia, congestive heart failure, electrocardiographic abnormalities (i.e., sinus node arrest, junctional bradycardia, high degree AV block and arrhythmias), orthostatic symptoms, palpitations, syncope, and tachycardia.
Central Nervous System: Agitation, anxiety, delirium, hallucinations (including visual and auditory), insomnia, mental depression, behavioral changes, paresthesia, sleep disorder, and vivid dreams or nightmares.
Gastrointestinal: Anorexia, constipation, nausea, and vomiting.
Hematologic: Thrombocytopenia.
Hepatobiliary: Hepatitis and transaminitis.
Hypersensitivity: Angioedema, hives, pruritus, rash, and urticaria.
Metabolic: Transient elevation of blood glucose or serum creatine phosphokinase, and weight gain.
Musculoskeletal: Leg cramps and muscle or joint pain.
Ophthalmological: Accommodation disorder, blurred vision, burning of the eyes, decreased lacrimation, and dryness of eyes.
Renal and Urinary: Difficulty in micturition, nocturia, and urinary retention.
Reproductive System and Breast Disorders: Gynecomastia. erectile dysfunction, and loss of libido.
Vascular: Raynaud's phenomenon.

7 DRUG INTERACTIONS

The interactions of JAVADIN with co-administration of other drugs have not been studied. The drug interaction data provided in this section is based on oral immediate-release clonidine formulations.
Table 1 displays clinically important drug interactions with JAVADIN.

Table 1: Clinically Important Drug Interactions with JAVADIN.

Antihypertensive drugs
Clinical Implication | Concomitant use of antihypertensive drugs with clonidine potentiates the hypotensive effects of clonidine [see Warnings and Precautions (5.1)].
Intervention | Monitor blood pressure and heart rate, and adjust dosage of JAVADIN accordingly in patients treated concomitantly with antihypertensives
CNS depressants
Clinical Implication | Concomitant use of CNS depressants with clonidine potentiates the sedating effects [see Warnings and Precautions (5.3)].
Intervention | Avoid concomitant use of CNS depressants with JAVADIN.
Drugs that affect sinus node function or AV node conduction (e.g., digitalis, calcium channel blockers, beta blockers)
Clinical Implication | Concomitant use of drugs that affect sinus node function or AV node conduction with clonidine potentiate bradycardia and risk of AV block [see Warnings and Precautions (5.1)].
Intervention | Avoid concomitant use of drugs that affect sinus node function or AV node conduction with JAVADIN.
Tricyclic antidepressants
Clinical Implication | Concomitant use of tricyclic antidepressants with clonidine can increase blood pressure and may counteract the hypotensive effects of clonidine.
Intervention | Monitor blood pressure and adjust dosage of JAVADIN as needed.

8 USE IN SPECIFIC POPULATIONS

8.1 Pregnancy

Risk Summary
Prolonged experience with clonidine in pregnant women over several decades, based on published literature, including controlled trials, a retrospective cohort study and case reports, have not identified a drug associated risk of major birth defects, miscarriage, adverse maternal or fetal outcomes. In animal embryofetal studies, increased resorptions were seen in rats and mice administered oral clonidine hydrochloride from implantation through organogenesis at approximately 2 times the maximum recommended human dose (MRHD) (see Data).
The estimated background risk of major birth defects and miscarriage for the indicated population is unknown. All pregnancies have a background risk of birth defect, loss, or other adverse outcomes. In the U.S. general population, the estimated background risk of major birth defects and miscarriages in clinically recognized pregnancies is 2 to 4% and 15 to 20%, respectively.
Data
Animal Data
Oral administration of clonidine hydrochloride to pregnant rabbits during the period of embryo/fetal organogenesis at doses of up to 0.08 mg/kg/day (approximately 0.6 times the oral maximum recommended human dose [MRHD] of 2.4 mg/day) produced no developmental effects. In pregnant rats, however, doses as low as 0.015 mg/kg/day (~1/16 the oral MRHD on a mg/kg basis) were associated with increased resorptions in a study in which dams were treated continuously from 2 months prior to mating and throughout gestation. Increased resorptions were not associated with treatment at the same or at higher dose levels when treatment of the dams was restricted to gestation days 6-15. Increases in resorptions were observed in both rats and mice at 0.5 mg/kg/day (2 and 1 times the MRHD in rats and mice, respectively) or higher when the animals were treated on gestation days 1-14; 0.5 mg/kg/day was the lowest dose employed in this study.

8.2 Lactation

Risk Summary
Based on published lactation studies, clonidine hydrochloride is present in human milk at relative infant doses ranging from 4.1 to 8.4% of the maternal weight-adjusted dosage. Although in most cases, there were no reported adverse effects in breastfed infants exposed to clonidine, there is one case report of sedation, hypotonia, and apnea in an infant exposed to clonidine through breast milk. If an infant is exposed to clonidine hydrochloride through breastmilk, monitor for symptoms of hypotension and bradycardia, such as sedation, lethargy, tachypnea and poor feeding (see Clinical Considerations). The developmental and health benefits of breastfeeding should be considered along with the mother’s clinical need for JAVADIN and any potential adverse effects on the breastfed child from clonidine or from the underlying maternal condition. Exercise caution when JAVADIN is administered to a nursing woman.
Clinical Considerations
Monitor breastfeeding infants exposed to JAVADIN through breast milk for symptoms of hypotension and/or bradycardia such as sedation, lethargy, tachypnea, and poor feeding.

8.4 Pediatric Use

Safety and effectiveness in pediatric patients have not been established.

8.6 Renal Impairment

The half-life of clonidine increases in patients with renal impairment [see Clinical Pharmacology (12.3)]. Patients with renal impairment may start from a lower dose. Since only a minimal amount of clonidine is removed during routine hemodialysis, there is no need to give supplemental JAVADIN following dialysis.

10 OVERDOSAGE

Hypertension may develop early and may be followed by hypotension, bradycardia, respiratory depression, hypothermia, drowsiness, decreased or absent reflexes, weakness, irritability and miosis. The frequency of CNS depression may be higher in pediatric patients than adults. Large overdoses may result in reversible cardiac conduction defects or dysrhythmias, apnea, coma and seizures. Signs and symptoms of overdose generally occur within 30 minutes to two hours after exposure. Dialysis is not likely to significantly enhance the elimination of clonidine.

11 DESCRIPTION

JAVADIN (clonidine hydrochloride) oral solution is a central alpha-2 adrenergic agonist hypotensive agent available as a 0.02 mg/mL solution for oral administration.
Clonidine hydrochloride is an imidazoline derivative and exists as a mesomeric compound. The chemical name is 2-(2,6-dichlorophenylamino)-2-imidazoline hydrochloride. Its molecular formula is C9H9Cl2N3, HCl which corresponds to a molecular weight of 266.5. The following is the structural formula:

Clonidine hydrochloride USP is a white or almost white crystalline powder. It is soluble in water, and ethanol and slightly soluble in Chloroform.
JAVADIN is a clear colorless oral solution. Each mL contains 0.02 mg of clonidine hydrochloride (equivalent to 0.0173 mg of clonidine). The inactive ingredients are: mixed berry flavor, purified water, sodium chloride, sodium propionate, sucralose.

12 CLINICAL PHARMACOLOGY

12.1 Mechanism of Action

Clonidine stimulates alpha-adrenoreceptors in the brain. Clonidine is not a central nervous system stimulant. Clonidine is a known antihypertensive agent. By stimulating alpha-adrenoreceptors in the brain stem, clonidine reduces sympathetic outflow from the central nervous system and decreases peripheral resistance, renal vascular resistance, heart rate, and blood pressure.

12.2 Pharmacodynamics

The patient’s blood pressure declines within 30 to 60 minutes after an oral dose, the maximum decrease occurring within 2 to 4 hours. Renal blood flow and glomerular filtration rate remain essentially unchanged. Normal postural reflexes are intact; therefore, orthostatic symptoms are mild and infrequent. The antihypertensive effect is reached at plasma concentrations between about 0.2 and 2.0 ng/mL in patients with normal excretory function. A further rise in the plasma levels will not enhance the antihypertensive effect.
Clonidine hydrochloride in humans have demonstrated a moderate reduction (15% to 20%) of cardiac output in the supine position with no change in the peripheral resistance: at a 45° tilt there is a smaller reduction in cardiac output and a decrease of peripheral resistance. During long term therapy, cardiac output tends to return to control values, while peripheral resistance remains decreased. Slowing of the pulse rate has been observed in most patients given clonidine but the drug does not alter normal hemodynamic response to exercise.
Tolerance to the antihypertensive effect may develop in some patients, necessitating a reevaluation of therapy.
Other studies in patients have provided evidence of a reduction in plasma renin activity and in the excretion of aldosterone and catecholamines. The exact relationship of these pharmacologic actions to the antihypertensive effect of clonidine has not been fully elucidated.

12.3 Pharmacokinetics

Median time to peak clonidine plasma concentrations (Cmax) occurred at approximately 2.8 hours (range: 1 to 6 hours) following 0.3 mg oral dose of JAVADIN in healthy adult subjects under fasting conditions. The pharmacokinetics of clonidine is dose-proportional in the range of 0.1 to 0.6 mg.
Absorption
The absolute bioavailability of clonidine on oral administration is 70% to 80%.
Effect of Food
Food had no effect on plasma exposures of clonidine after administration of JAVADIN.
Distribution
Following intravenous administration, clonidine displays biphasic disposition with a distribution half-life of about 20 minutes. Clonidine crosses the placental barrier.
Elimination
Elimination half-life ranges from 12 to 16 hours.
Metabolism
About 50% of the absorbed dose is metabolized in the liver.
Excretion
Following oral administration, about 40% to 60% of the absorbed dose is recovered in the urine as unchanged drug in 24 hours.
Specific Populations
Patients with Renal Impairment
The half-life increases up to 41 hours in patients with severe impairment of renal function.
Clonidine is minimally removed during hemodialysis.

13 NONCLINICAL TOXICOLOGY

13.1 Carcinogenesis, Mutagenesis, Impairment of Fertility

Carcinogenesis
Chronic dietary administration of clonidine was not carcinogenic to rats (132 weeks) or mice (78 weeks) dosed, respectively, at up to 10 or 15 times the maximum recommended daily human dose as mg/kg (2 or 1 times the MRDHD on a mg/m^2 basis).
Mutagenicity
There was no evidence of genotoxicity in the Ames test for mutagenicity or mouse micronucleus test for clastogenicity.
Impairment of Fertility
In a reproduction study fertility of female rats appeared to be adversely affected at dose levels of 0.5 and 2.0 mg/kg/day (2 and 8 times the MRHD on a mg/m^2 basis). Lower doses have not been adequately evaluated and a no adverse effect level could not be established.

16 HOW SUPPLIED/STORAGE AND HANDLING

16.1 How Supplied

JAVADIN (clonidine hydrochloride) is a clear, colorless solution supplied in a high-density polyethylene (HDPE) bottle with child-resistant closure. The 0.02 mg/mL oral solution is available in bottles of 250 mL (NDC 24338-115-01).

16.2 Storage and Handling

Store at 20°C to 25°C (68°F to 77°F); excursions permitted between 15°C and 30°C (59°F and 86° F) (see USP Controlled Room Temperature).
Discard unused portion 60 days after first opening.

17 PATIENT COUNSELING INFORMATION

Sedation and Somnolence
Advise patients not to interrupt JAVADIN therapy without consulting their physician. They should be cautious of potential sedative effects, dizziness, or accommodation issues and avoid activities such as driving or operating machinery. Additionally, advise patients that the sedative effects may be increased by the use of alcohol, barbiturates, or other sedating drugs. [see Drug Interactions (7) and Warnings and Precautions (5.3)].
Rebound Hypertension
Advise patients not to discontinue Clonidine therapy without consulting their physician, as sudden cessation can cause symptoms like tachycardia, rapid blood pressure elevation, headache, nervousness and agitation. The risk is higher with higher doses or ongoing beta-blocker use. [see Warnings and Precautions (5.2)].
Bradycardia, cardiac conduction abnormalities, and symptomatic hypotension
Advise patients who have a history of syncope or may have a condition that predisposes them to syncope, such as symptomatic hypotension, bradycardia, or dehydration, to avoid becoming dehydrated or overheated.
Administration Information
Instruct patients or caregivers to use an oral dosing syringe or oral dosing cup to correctly measure the prescribed amount of medication. Inform patients that oral dosing syringes may be obtained from their pharmacy.

Manufactured for:
Azurity Pharmaceuticals, Inc.
Woburn, MA 01801

PACKAGE LABEL.PRINCIPAL DISPLAY PANEL

NDC 24338-115-01

JAVADINTM (clonidine HCl) Oral Solution - Carton Label

0.02 mg/mL

JAVADINTM (clonidine HCl) Oral Solution - Container Label

0.02 mg/mL